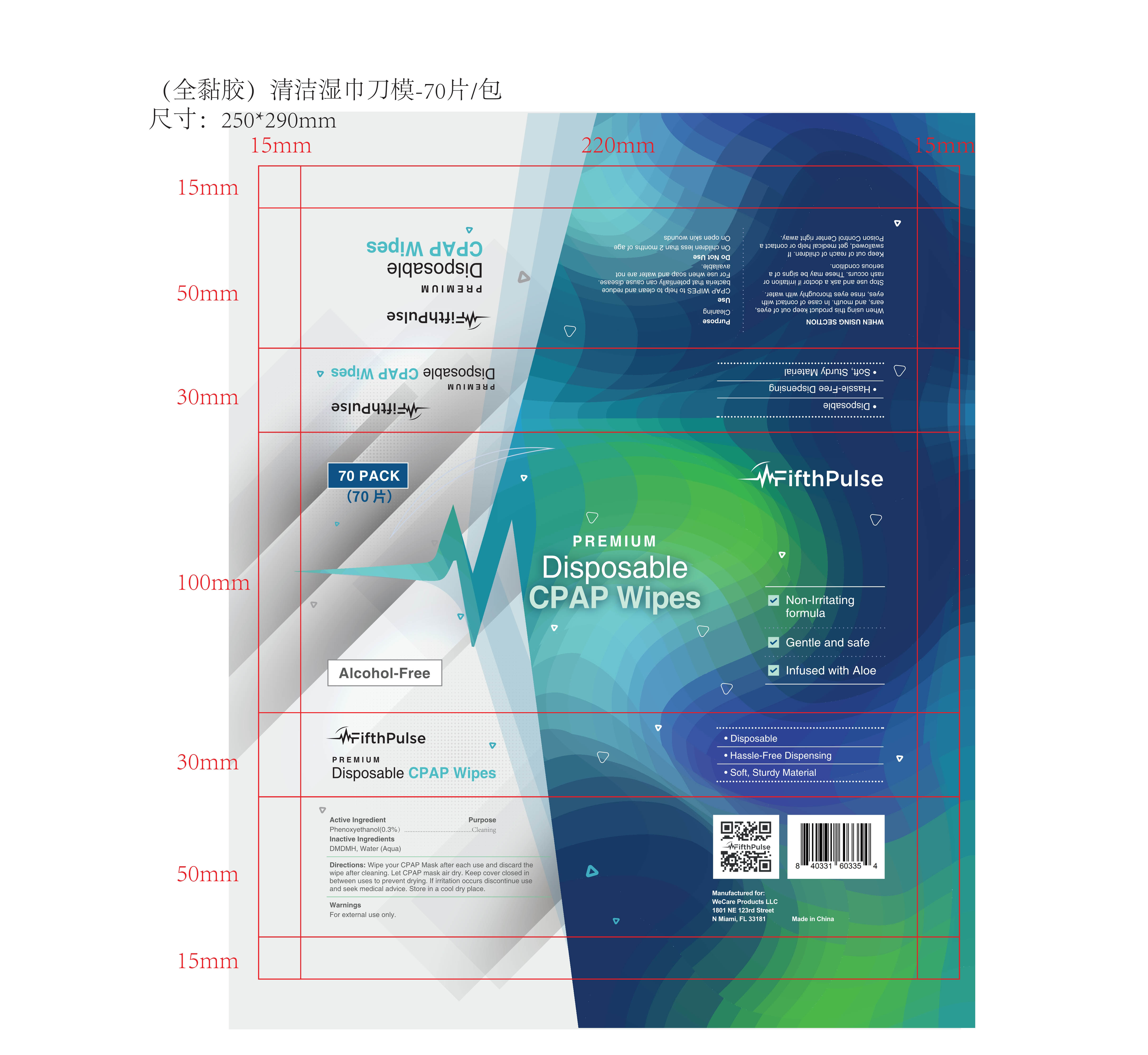 DRUG LABEL: CPAP WIPES
NDC: 43116-031 | Form: CLOTH
Manufacturer: Shenzhen Shierjie Biological Engineering Co., LTD
Category: otc | Type: HUMAN OTC DRUG LABEL
Date: 20250209

ACTIVE INGREDIENTS: PHENOXYETHANOL 0.3 g/100 1
INACTIVE INGREDIENTS: WATER; HYDANTOIN

43116-031
CPAP WIPES

Active Ingredient

Phenoxyethanol 0.3%

Purpose

Cleaning

Uses

CPAP WIPES to help to clean and reduce bacteria that potentially can cause disease.
For use when soap and water are not available.

Warnings

For external use only.

Do not use

On children less than 2 months of age
On open skin wounds

When using this product keep out of eyes, ears, and mouth. In case of contact with eyes, rinse eyes thoroughly with water.
Stop use and ask a doctor if irritation or rash occurs. These may be signs of a serious condition.
Keep out of reach of children. If swallowed, get medical help or contact a Poison Control Center right away.

Stop use and ask a doctor if irritation or rash occurs. These may be signs of a serious condition.

Keep out of reach of children

Kep out of reach of children. If swallowed, get medical help or contact a Poison Control Center right away.

Directions

Wipe your CPAP Mask after each use and discard the wipe after cleaning. Let CPAP mask air dry. Keep cover closed in between uses to prevent drying. If irritation occurs discontinue use and seek medical advice. Store in a cool dry place.

Other information

-N/A

Inactive ingredients

DMDMH, Water (Aqua)